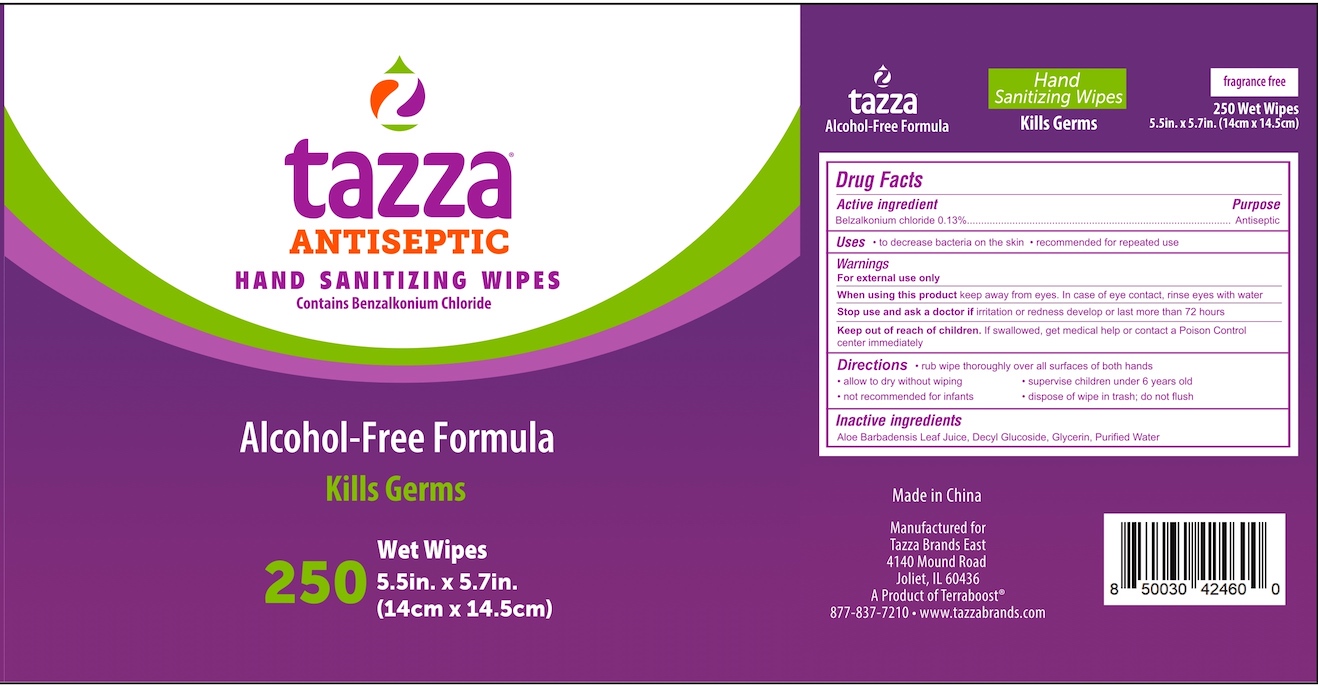 DRUG LABEL: Tazza Antiseptic Hand Sanitizing Wipes
NDC: 76370-0019 | Form: CLOTH
Manufacturer: Tazza Brands East, Inc.
Category: otc | Type: HUMAN OTC DRUG LABEL
Date: 20240124

ACTIVE INGREDIENTS: BENZALKONIUM CHLORIDE 0.13 g/100 mL
INACTIVE INGREDIENTS: WATER; GLYCERIN; ALOE VERA LEAF; DECYL GLUCOSIDE

Tazza Antiseptic Hand Sanitizing Wipes (14 cm x 14.5 cm)

Drug Facts

Active ingredient

Benzalkonium chloride 0.13%

Purpose

Antiseptic

Uses

- to decrease bacteria on the skin
- recommended for repeated use

Warnings

For external use only

When using this product keep away from eyes. In case of eye contact, rinse eyes with water.

Stop use and ask a doctor if irritation or redness develop or last more than 72 hours

Keep out of reach of children. If swallowed, get medical help or contact a Poison Control Center immediately.

Directions

- rub wipe thoroughly over all surfaces of both hands
- allow to dry without wiping
- supervise children under 6 years old
- not recommended for infants
- dispose of wipe in trash; do not fliush

INACTIVE INGREDIENT

Inactive ingredients Aloe Barbadensis Leaf Juice, Decyl Glucoside, Glycerin, Purified Water

Made in China

Manufactured for

Tazza Brands East

4140 Mound Road

Joliet, IL 60436

A Product of Terraboost®

877-837-7210 • www.tazzabrands.com

PACKAGE LABEL

tazza®

ANTISEPTIC HAND SANITIZING WIPES

Contains Benzalkonium Chloride

Alcohol-Free Formula

Kills Germs

250 Wet Wipes

5.5in. x 5.7in (14cm x 14.5cm)